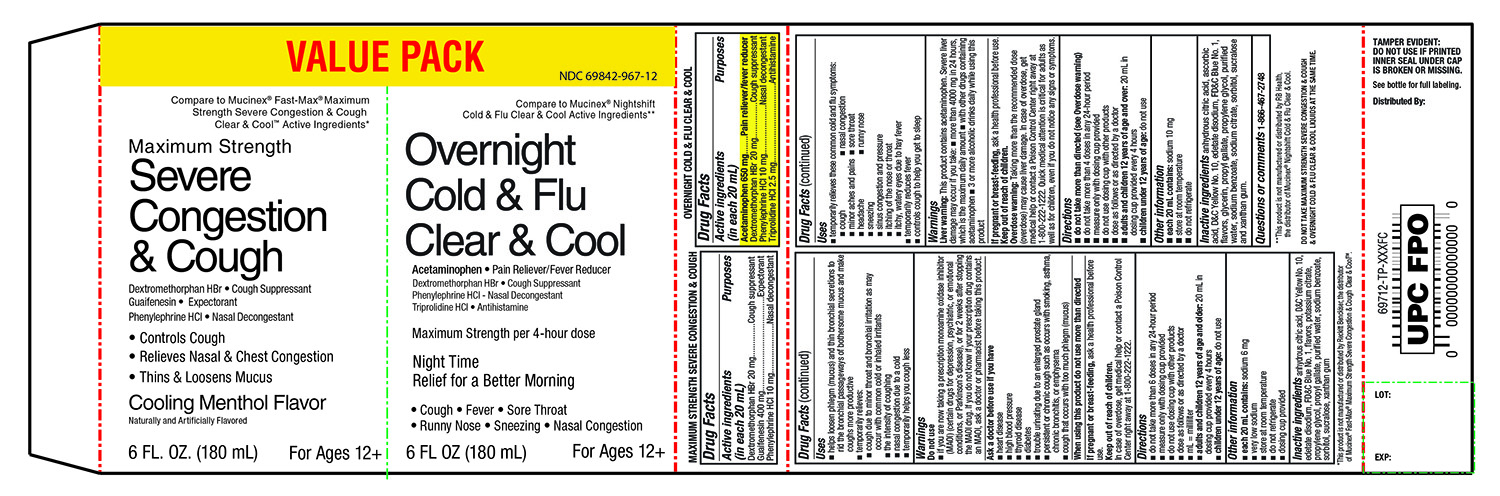 DRUG LABEL: CVS Maximum Strength Severe Congestion and Cough
NDC: 69842-967 | Form: KIT | Route: ORAL
Manufacturer: CVS
Category: otc | Type: HUMAN OTC DRUG LABEL
Date: 20200413

ACTIVE INGREDIENTS: Dextromethorphan Hydrobromide 20 mg/20 mL; Guaifenesin 400 mg/20 mL; PHENYLEPHRINE HYDROCHLORIDE 10 mg/20 mL; Acetaminophen 650 mg/20 mL; DEXTROMETHORPHAN HYDROBROMIDE 20 mg/20 mL; PHENYLEPHRINE HYDROCHLORIDE 10 mg/20 mL; TRIPROLIDINE HYDROCHLORIDE 2.5 mg/20 mL
INACTIVE INGREDIENTS: ANHYDROUS CITRIC ACID; D&C YELLOW NO. 10; EDETATE DISODIUM; FD&C Blue No. 1; POTASSIUM CITRATE; propylene glycol; propyl gallate; water; sodium benzoate; sorbitol; sucralose; xanthan gum; anhydrous citric acid; ASCORBIC ACID; D&C YELLOW NO. 10; edetate disodium; FD&C Blue No. 1; glycerin; propyl gallate; propylene glycol; water; sodium benzoate; SODIUM CITRATE, UNSPECIFIED FORM; sorbitol; sucralose; xanthan gum

Maximum Strength Severe Congestion & Cough and Overnight Cold & Flu Value Pack

Drug Facts

ACTIVE INGREDIENT

PURPOSE

Active ingredients (in each 20 mL) Maximum Strength Severe Congestion & Cough | Purposes
Dextromethorphan HBr 20 mg | Cough suppressant
Guaifenesin 400 mg; Phenylephrine HCl 10 mg | Expectorant; Nasal decongestant

Active ingredients (in each 20 mL) | Purposes
Overnight Cold & Flu Clear & Cool
Acetaminophen 650 mg | Pain reliever/fever reducer
Dextromethorphan HBr 20 mg; Phenylephrine HCl 10 mg | Antihistamine/cough suppressant; Nasal decongestant
Triprolidine HCl 2.5 mg | Antihistamine

Uses

MAXIMUM STRENGTH SEVERE CONGESTION & COUGH

- helps loosen phlegm (mucus) and thin bronchial secretions to rid the bronchial passageways of bothersome mucus and make coughs more productive
- temporarily relieves
  - cough due to minor throat and bronchial irritation as may occur with the common cold or inhaled irritants
  - the intensity of coughing
  - nasal congestion due to a cold
  - temporarily helps you cough less

Warnings

Do not use

- if you are now taking a prescription monoamine oxidase inhibitor (MAOI) (certain drugs for depression, psychiatric, or emotional conditions, or Parkinson's disease), or for 2 weeks after stopping the MAOI drug. If you do not know if your prescription drug contains an MAOI, ask a doctor or pharmacist before taking this product.

Ask a doctor before use if you have

- heart disease
- high blood pressure
- thyroid disease
- diabetes
- trouble urinating due to an enlarged prostate gland
- persistent or chronic cough such as occurs with smoking, asthma, chronic bronchitis or emphysema
- cough that occurs with too much phlegm (mucus)

Keep Out of Reach of Children

In case of overdose, get medical help or contact a Poison control Centre right away at 1-800-222-1222

Directions

- do not take more than 6 doses in any 24-hour period
- measure only with dosing cup provided
- do not use dosing cup with other products
- dose as follows or as directed by a doctor
- mL = milliliter
- adults and children 12 years of age and older: 20 mL in dosing cup provided every 4 hours
- children under 12 years of age: do not use

Other information

- each 20 mL contains: sodium 6 mg
- low sodium
- store at room temperature
- do not refrigerate
- dosing cup provided

Inactive ingredients (Maximum strength mucus relief DM)

anhydrous citric acid, D&C Yellow No. 10, edetate disodium, FD&C Blue No.1, flavors, potassium citrate, propylene glycol, propyl gallate, purified water, sodium benzoate, sorbitol, sucralose, xanthan gum

Uses (OVERNIGHT COLD & FLU CLEAR & COOL

- temporarily relieves these common cold and flu symptoms:
- cough
- nasal congestion
- minor aches and pains
- sore throat
- headache
- runny nose
- sneezing
- itching of the nose or throat
- itchy, watery eyes due to hay fever
- temporarily reduces fever
- controls cough to help you get to sleep

Warnings

Liver warnings: This product contains acetaminophen. Severe liver damage may occur if you take\

- more than 4000 mg in 24 hours, which is the maximum daily amount
- with other drugs containing acetaminophen
- 3 or more alcoholic drinks daily while using this product

If pregnant or breast feeding

ask a health professional before use

Keep Out of Reach of Children

Overdose warning: Taking more than the recommended dose (overdose) may cause liver damage. In case of overdose, get medical help or contact a Poison Control Centre right away at 1-800-222-1222.

Quick medical attention is critical for adults as well as for children, even if you do not notice any signs

Directions

- do not take more than directed (see overdose warnings
- do not take more than 4 doses in any 24-hour period
- measure only with dosing cup provided
- do not use dosing cup with other products
- dose as follows or as directed by a doctor
- adults and children 12 years of age and over: 20 ml in dosing cup provided every 4 hours
- children under 12 years of age: do not use

Other Information

- each 20 mL contains: sodium 10 mg
- store at room temperature
- do not refrigerate

Inactive ingredients (Overnight Cold & Flu)

anhydrous citric acid, ascorbic acid, D&C Yellow No. 10, edetate disodium, FD&C Blue No. 1, flavors, glycerin, propyl gallate, propylene glycol, purified water, sodium benzoate, sodium citrate, sorbitol, sucralose and xanthan gum

Questions or comments?

(1-866-467-2748)

PRINCIPAL DISPLAY PANEL - Kit Carton

VALUE PACK

NDC 69842-967-12

Compare to Mucinex® Fast Max® DM Maximum Strength Severe Congestion & Cough Clear & Cool™ Active Ingredients*

Maximum Strength

Severe Congestion & Cough

Dextromethorphan HBr • Cough Suppressant
Guaifenesin • Expectorant

Phenylephrine HCl • Nasal Decongestant

- Controls Cough
- Relieves Nasal & Chest Congestion
- Thins & Loosens Mucus

Cooling Menthol Flavor

Naturally and Artificially Flavored

For Ages 12+

6 FL. OZ. (180 mL)

*This product is not manufactured or distributed by Reckitt Benckiser, the distributor of Mucinex® Fast-Max® Maximum Strength Severe Congestion & Cough Clear & Cool™

Compare to Mucinex® Nightshift Cold & Flu Clear & Cool Active Ingredients**

Overnight Cold & Flu

Clear & Cool

Acetaminophen • Pain Reliever/Fever Reducer
Dextromethorphan HBr • Cough Suppressant
Phenylephrine HCl • Nasal Decongestant

Triprolidine HCl • Antihistamine

Maximum Strength per 4-hour dose

Night Time Relief for a Better Morning

- Cough
- Fever
- Sore Throat
- Runny Nose
- Sneezing
- Nasal Congestion

For Ages 12+

6 FL OZ (180 mL)

**This product is not manufactured or distributed by RB Health, the distributor of Mucinex® Nightshift Cold & Flu Clear & Cool.

DO NOT TAKE MAXIMUM STRENGTH SEVERE CONGESTION & COUGH & OVERNIGHT COLD & FLU CLEAR & COOL LIQUIDS AT THE SAME TIME.